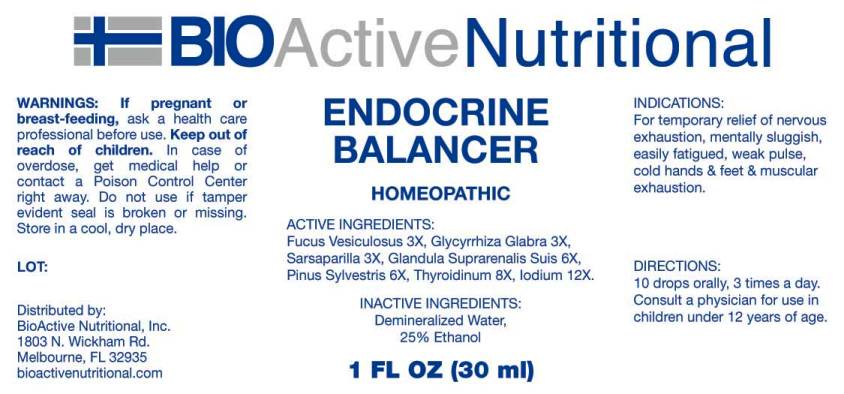 DRUG LABEL: Endocrine Balancer
NDC: 43857-0024 | Form: LIQUID
Manufacturer: BioActive Nutritional, Inc.
Category: homeopathic | Type: HUMAN OTC DRUG LABEL
Date: 20240208

ACTIVE INGREDIENTS: FUCUS VESICULOSUS 3 [hp_X]/1 mL; GLYCYRRHIZA GLABRA 3 [hp_X]/1 mL; SMILAX ORNATA ROOT 3 [hp_X]/1 mL; SUS SCROFA ADRENAL GLAND 6 [hp_X]/1 mL; PINUS SYLVESTRIS LEAFY TWIG 6 [hp_X]/1 mL; THYROID 8 [hp_X]/1 mL; IODINE 12 [hp_X]/1 mL
INACTIVE INGREDIENTS: ALCOHOL; WATER

DRUG FACTS:

ACTIVE INGREDIENTS:

Fucus Vesiculosus 3X, Glycyrrhiza Glabra 3X, Sarsaparilla 3X, Glandula Suprarenalis Suis 6X, Pinus Sylvestris 6X, Thyroidinum (Suis) 8X, Iodium 12X.

INDICATIONS:

For temporary relief of nervous exhaustion, mentally sluggish, easily fatigued, weak pulse, cold hands and feet and muscular exhaustion.

WARNINGS:

If pregnant or breast-feeding, ask a health care professional before use.

Keep out of reach of children. In case of overdose, get medical help or contact a Poison Control Center right away.

Do not use if tamper evident seal is broken or missing.

Store in a cool, dry place.

DIRECTIONS:

10 drops orally, 3 times a day. Consult a physician for use in children under 12 years of age.

INACTIVE INGREDIENTS:

Demineralized Water, 25% Ethanol.

KEEP OUT OF REACH OF CHILDREN:

In case of overdose, get medical help or contact a Poison Control Center right away.

INDICATIONS:

For temporary relief of nervous exhaustion, mentally sluggish, easily fatigues, weak pulse, cold hands and feet and muscular exhaustion.

QUESTIONS:

Distributed by:

BioActive Nutritional, Inc.

1803 N. Wickham Rd.

Melbourne, FL 32935

bioactivenutritional.com

PACKAGE LABEL DISPLAY:

BIOActive Nutritional

ENDOCRINE

BALANCER

HOMEOPATHIC

1 FL OZ (30 ml)